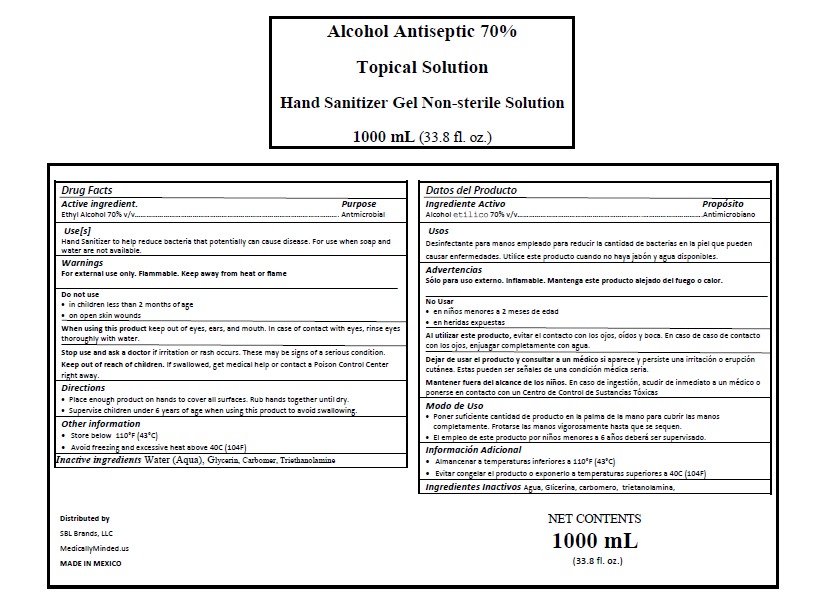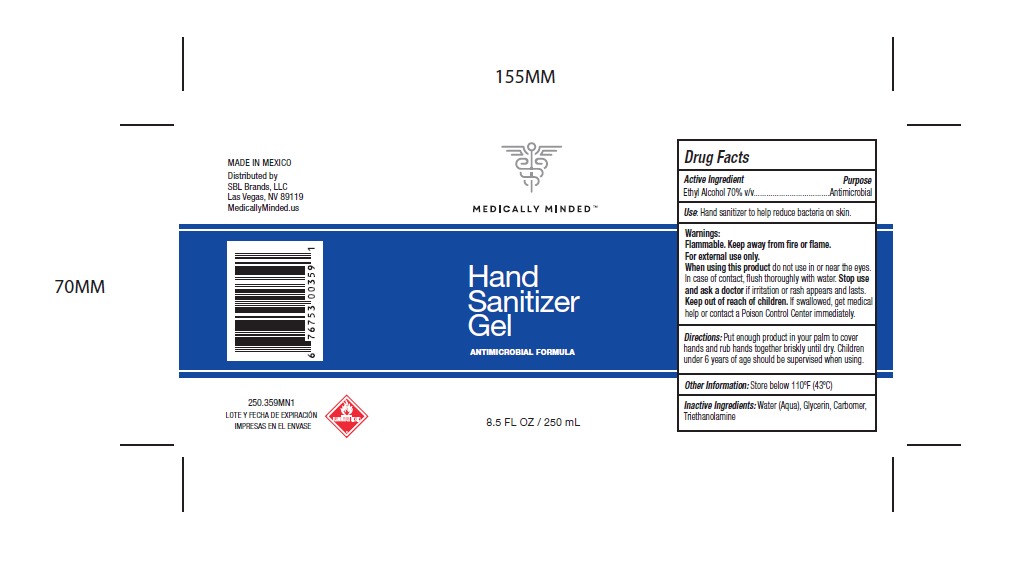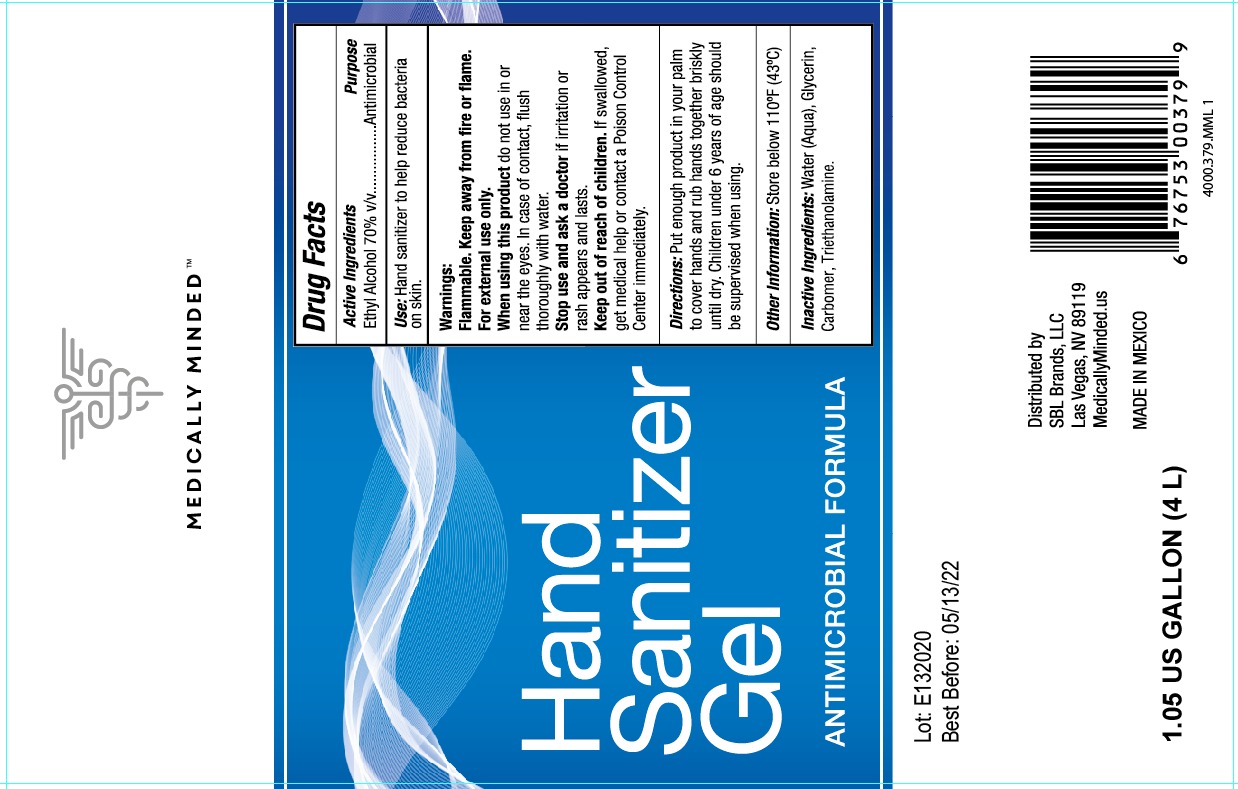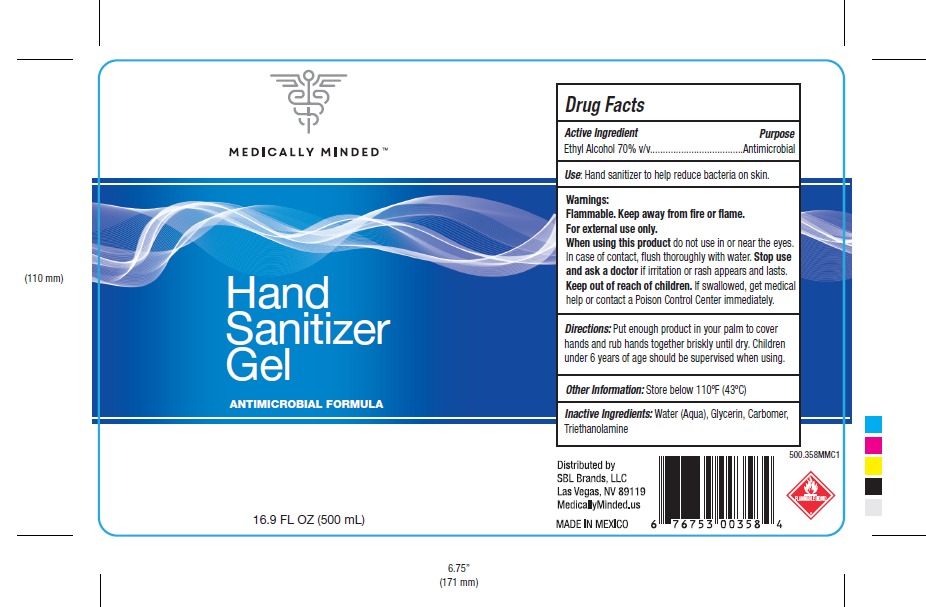 DRUG LABEL: HAND SANITIZER
NDC: 79049-0030 | Form: GEL
Manufacturer: Casillas Tiscareno, María Guadalupe
Category: otc | Type: HUMAN OTC DRUG LABEL
Date: 20200616

ACTIVE INGREDIENTS: ALCOHOL 0.7 mL/1 mL
INACTIVE INGREDIENTS: WATER 0.2922 mL/1 mL; GLYCERIN 0.00375 mL/1 mL; TRIETHANOLAMINE CAPROYL GLUTAMATE 0.00185 mL/1 mL; CARBOMER 940 0.0022 mL/1 mL

HAND SANITIZER GEL

DIRECTIONS

Place enough product on hands to cover all surfaces. Rub hands together until dry.

INACTIVE INGREDIENTS

Inactive ingredients Water (Aqua), Glycerin, Carbomer, Triethanolamine

INDICATIONS AND USAGE

Use[s]

Hand Sanitizer to help reduce bacteria that potentially can cause disease. For use when soap and water are not available.

Keep out of reach of children. If swallowed, get medical help or contact a Poison Control Center right away.

PURPOSE

Purpose Antmicrobial

WARNINGS AND PRECAUTIONS

Store below 110°F (43°C)

Avoid freezing and excessive heat above 40C (104F)

in children less than 2 months of age
on open skin wounds

WARNINGS

For external use only. Flammable. Keep away from heat or flame

ACTIVE INGREDIENT

Active ingredient Ethyl Alcohol 70% v/v…

Stop use and ask a doctor if irritation or rash occurs. These may be signs of a serious condition.